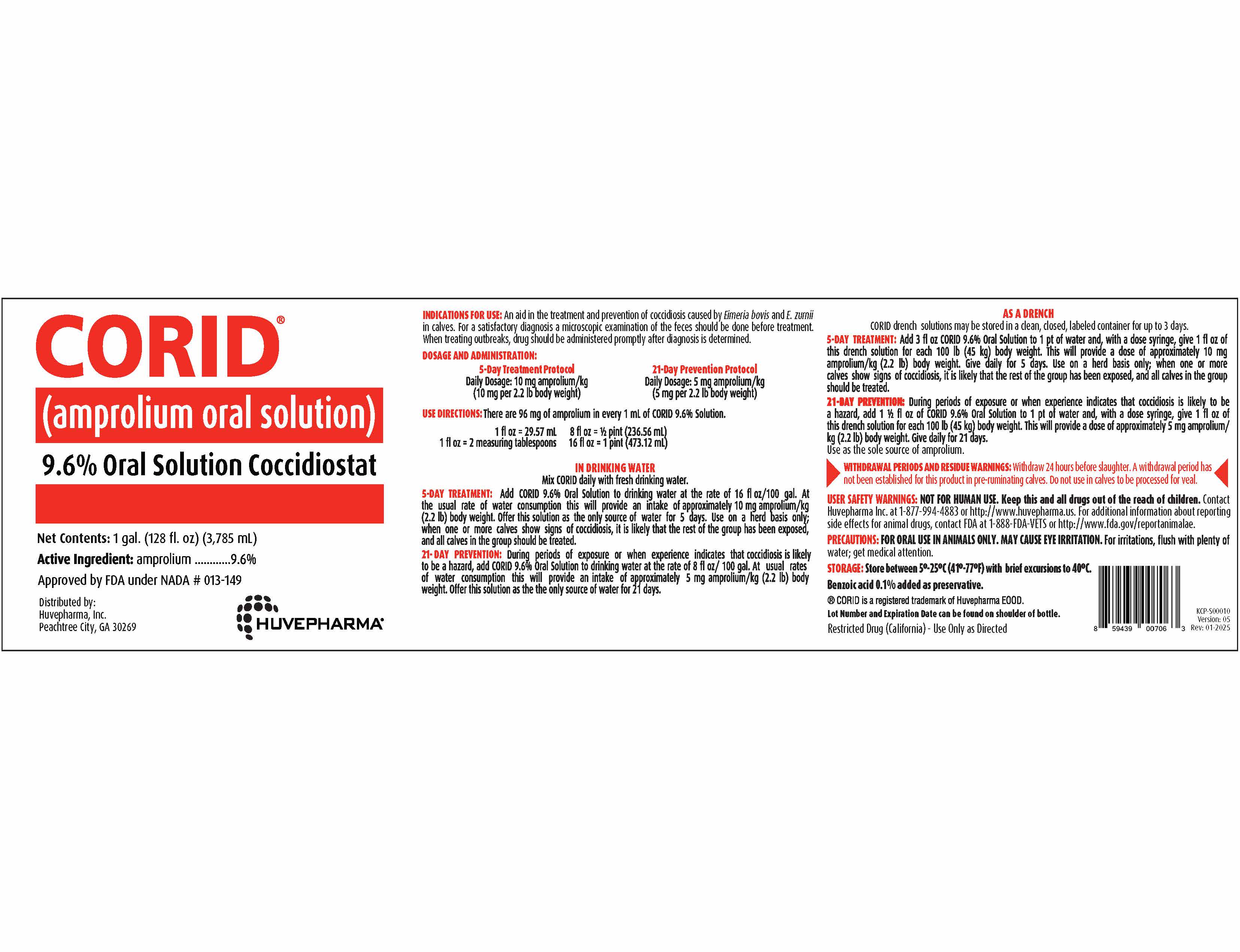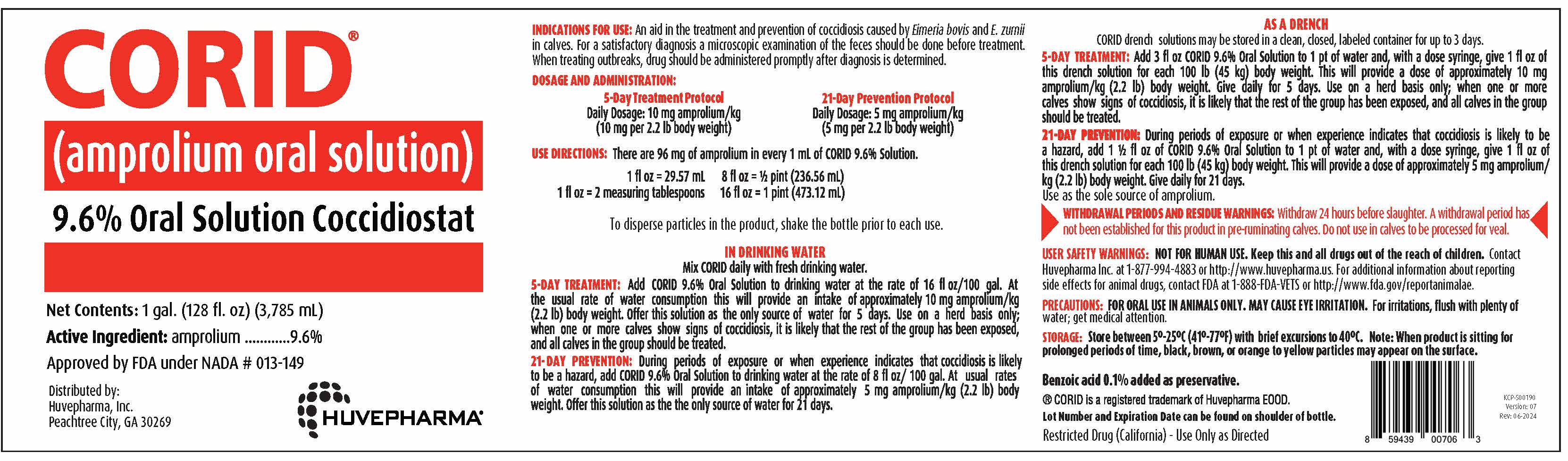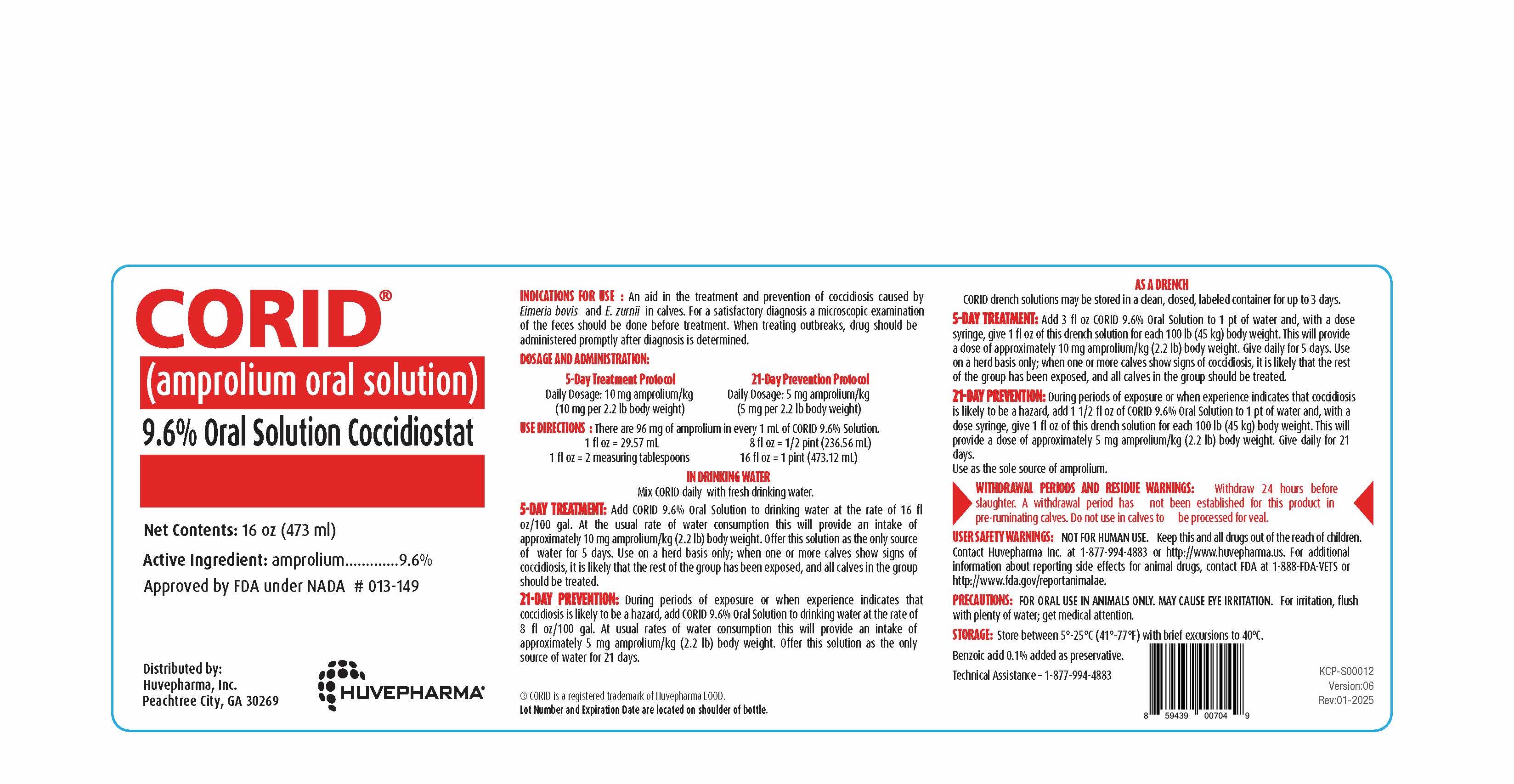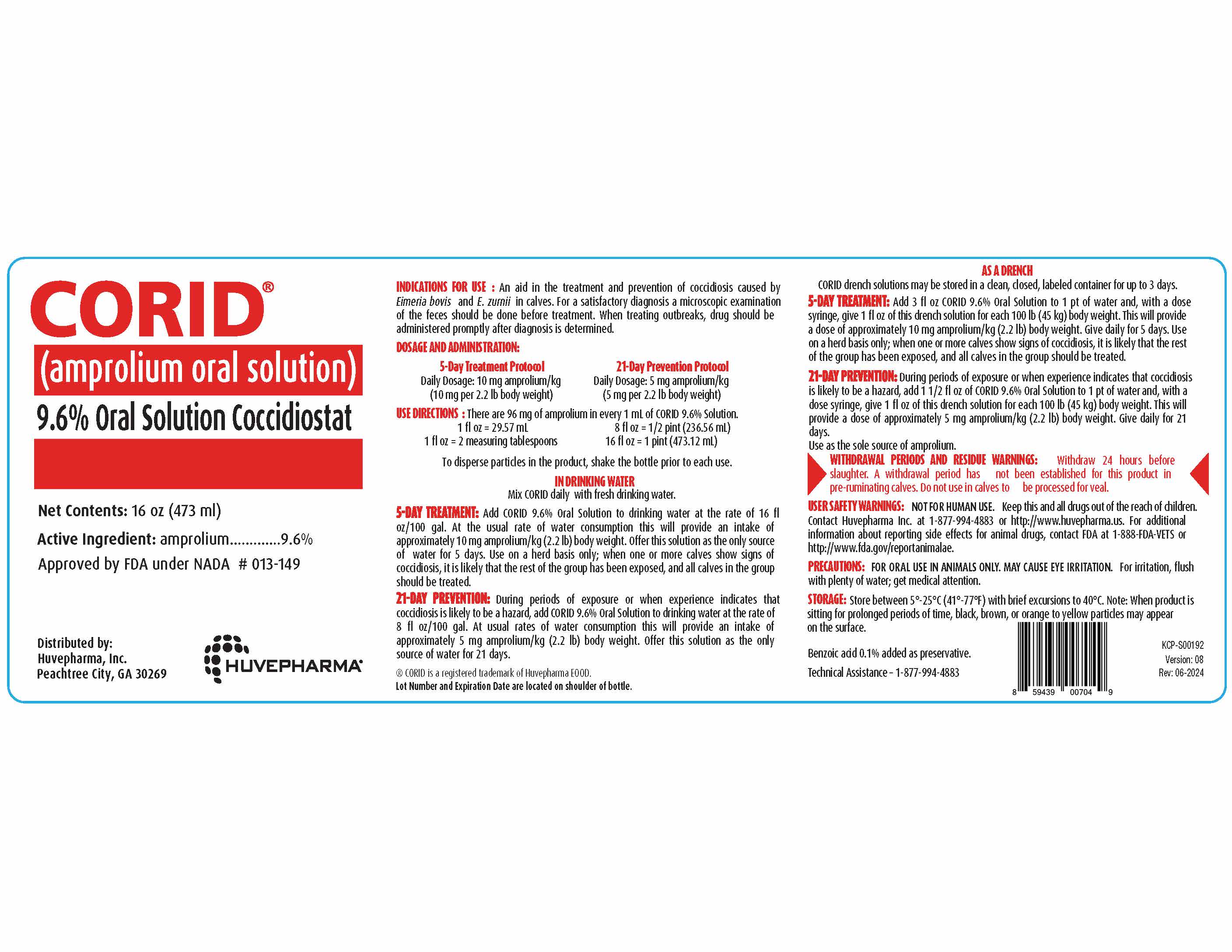 DRUG LABEL: CORID
NDC: 23243-2140 | Form: SOLUTION
Manufacturer: Huvepharma, Inc
Category: animal | Type: OTC ANIMAL DRUG LABEL
Date: 20250212

ACTIVE INGREDIENTS: amprolium 96 mg/1 mL

CORID®
(amprolium oral solution)
9.6% Oral Solution Coccidiostat

Net Contents: 1 gal. (128 fl. oz) (3,785 mL)

Active Ingredient: amprolium ............ 9.6%

Approved by FDA under NADA # 013-149

Distributed by: Huvepharma®
Huvepharma, Inc.
Peachtree City, GA 30269

VETERINARY INDICATIONS

INDICATIONS FOR USE: An aid in the treatment and prevention of coccidiosis caused by
Eimeria bovis and E. zurnii in calves. For a satisfactory diagnosis a microscopic examination
of the feces should be done before treatment. When treating outbreaks, drug should be
administered promptly after diagnosis is determined.

DOSAGE AND ADMINISTRATION:

5-Day Treatment Protocol 21-Day Prevention Protocol
Daily Dosage: 10 mg amprolium/kg Daily Dosage: 5 mg amprolium/kg
(10 mg per 2.2 lb body weight) (5 mg per 2.2 lb body weight)

INSTRUCTIONS FOR USE

USE DIRECTIONS: There are 96 mg of amprolium in every 1 mL of CORID 9.6% Solution.

1 fl oz = 29.57 mL 8 fl oz = 1/2 pint (236.56 mL)
1 fl oz = 2 measuring tablespoons 16 fl oz = 1 pint (473.12 mL)

To disperse particles in the product, shake the bottle prior to each use.

INSTRUCTIONS FOR USE

IN DRINKING WATER

Mix CORID daily with fresh drinking water.

5-DAY TREATMENT: Add CORID 9.6% Oral Solution to drinking water at the rate of 16 fl
oz/100 gal. At the usual rate of water consumption this will provide an intake of
approximately 10 mg amprolium/kg (2.2 lb) body weight. Offer this solution as the only source
of water for 5 days. Use on a herd basis only; when one or more calves show signs of
coccidiosis, it is likely that the rest of the group has been exposed, and all calves in the group
should be treated.

21-DAY PREVENTION: During periods of exposure or when experience indicates that
coccidiosis is likely to be a hazard, add CORID 9.6% Oral Solution to drinking water at the
rate of 8 fl oz/100 gal. At usual rates of water consumption this will provide an intake of
approximately 5 mg amprolium/kg (2.2 lb) body weight. Offer this solution as the only
source of water for 21 days.

AS A DRENCH
CORID drench solutions may be stored in a clean, closed, labeled container for up to 3 days.

5-DAY TREATMENT: Add 3 fl oz CORID 9.6% Oral Solution to 1 pt of water and, with a dose
syringe, give 1 fl oz of this drench solution for each 100 lb (45 kg) body weight. This will provide
a dose of approximately 10 mg amprolium/kg (2.2 lb) body weight. Give daily for 5 days. Use
on a herd basis only; when one or more calves show signs of coccidiosis, it is likely that the rest
of the group has been exposed, and all calves in the group should be treated.

21-DAY PREVENTION: During periods of exposure or when experience indicates that coccidiosis
is likely to be a hazard, add 1 1/2 fl oz of CORID 9.6% Oral Solution to 1 pt of water and, with a
dose syringe, give 1 fl oz of this drench solution for each 100 lb (45 kg) body weight. This will
provide a dose of approximately 5 mg amprolium/kg (2.2 lb) body weight. Give daily for 21
days. Use as the sole source of amprolium.

RESIDUE WARNING

WITHDRAWAL PERIODS AND RESIDUE WARNINGS: Withdraw 24 hours before slaughter. A withdrawal period has
not been established for this product in pre-ruminating calves. Do not use in calves to be processed for veal.

WARNINGS

USER SAFETY WARNINGS: NOT FOR HUMAN USE. Keep this and all drugs out of the reach of children.
Contact Huvepharma Inc. at 1-877-994-4883 or http://www.huvepharma.us. For additional information
about reporting side effects for animal drugs, contact FDA at 1-888-FDA-VETS or
http://www.fda.gov/reportanimalae.

PRECAUTIONS

PRECAUTIONS: FOR ORAL USE IN ANIMALS ONLY. MAY CAUSE EYE IRRITATION. For irritation, flush with
plenty of water; get medical attention.

STORAGE AND HANDLING

STORAGE: Store between 5°-25°C (41°- 77°F) with brief excursions to 40°C. Note: When product
is sitting for prolonged periods of time, black, brown, or orange to yellow particles may appear on
the surface.
Benzoic acid 0.1% added as preservative.

®CORID is a registered trademark of Huvepharma EOOD

Lot Number and Expiration Date can be found on shoulder of bottle.

Restricted Drug (California) - Use Only as Directed

KCP-S00190
Version: 07
Rev: 06-2024